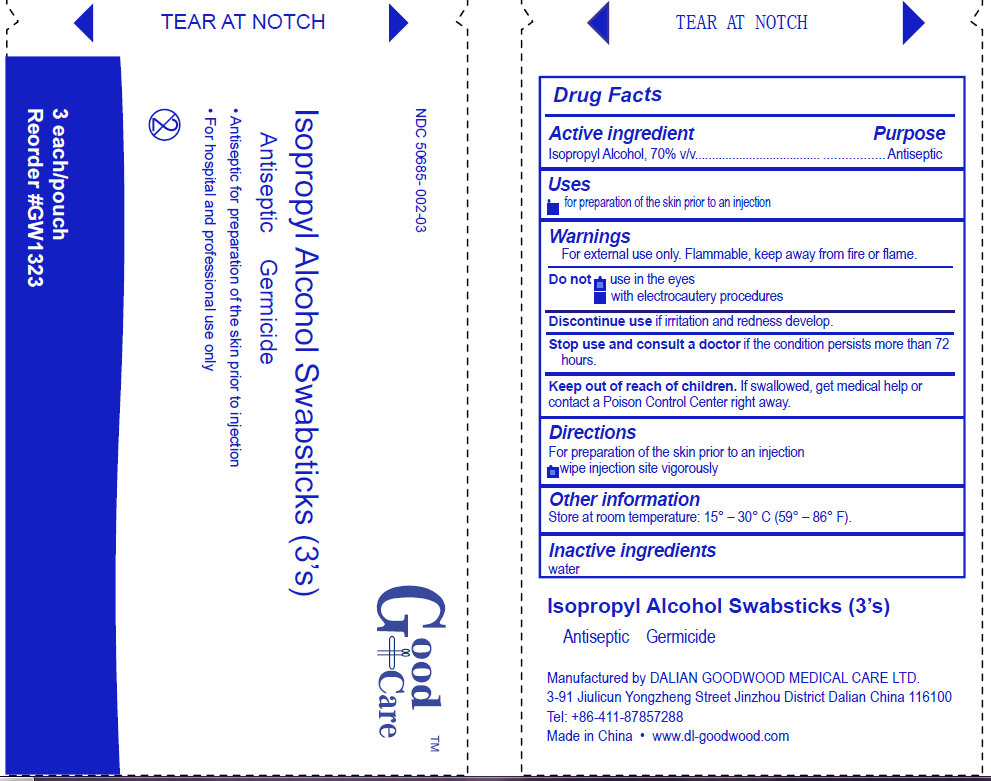 DRUG LABEL: Good Care Isopropyl Alcohol
NDC: 50685-002 | Form: SWAB
Manufacturer: Dalian Goodwood Medical Care Ltd.
Category: otc | Type: HUMAN OTC DRUG LABEL
Date: 20230525

ACTIVE INGREDIENTS: ISOPROPYL ALCOHOL 70 mL/100 mL
INACTIVE INGREDIENTS: WATER

Isopropyl Alcohol Swabsticks

Active Ingredient

Isopropyl Alcohol, 70% v/v

Purpose

Antiseptic

Uses

for preparation of the skin prior to an injection

Warnings

For external use only. Flammable, keep away from fire or flame

Do not use in the eyes with electrocautery procedures

Discontinue use if irritation and redness develop.

Stop use and consult a doctor if the condition persists more than 72 hours.

Keep out of reach of children. If swallowed, get medical help or contact a Poison Control Center right away.

Directions

For preparation of the skin prior to an injection

- wipe injection site vigorously

Other information

Store at room temperature: 15 degrees - 30 degrees C (59 degrees - 86 degrees F)

Inactive ingredients

water

Isopropyl Alcohol Swabsticks (3's)

Antiseptic Germicide

Manufactured by DALIAN GOODWOOD MEDICAL CARE LTD.

3-91 Jiulicun Yongzheng Street Jinzhou District Dalian China 116100

Tel: +86-411-87857288

Made in China www.dl-goodwood.com

PACKAGE LABEL

Good Care

Isopropyl Alcohol Swabsticks (3's)

Antiseptic Germicide

Antiseptic for preparation of the skin prior to injection
For hospital and professional use only